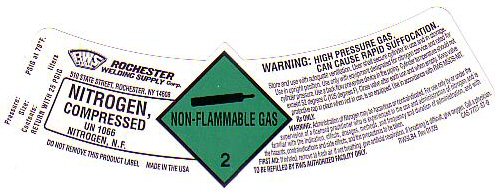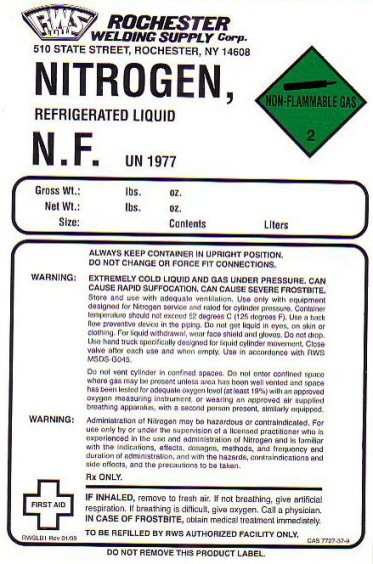 DRUG LABEL: NITROGEN
NDC: 53828-006 | Form: GAS
Manufacturer: Rochester Welding Supply Corp.
Category: prescription | Type: HUMAN PRESCRIPTION DRUG LABEL
Date: 20100101

ACTIVE INGREDIENTS: NITROGEN 99 L/100 L

NITROGEN COMPRESSED LABEL

NITROGEN COMPRESSED UN 1066 NITROGEN NF NON-FLAMMABLE-2

WARNING: HIGH PRESSURE GAS. CAN CAUSE RAPID SUFFOCATION. STORE AND USE WITH ADEQUATE VENTILATION. USER SHALL SECURE CYLINDER IN USE AND IN STORAGE. USE IN UPRIGHT POSITION. USE ONLY WITH EQUIPMENT DESIGNATED FOR NITROGEN SERVICE AND RATED FOR CYLINDER PRESSURE. USE A BACK FLOW PREVENTATIVE DEVICE IN THE PIPING. CYLINDER TEMPERATURE SHOULD NOT EXCEED 52 DEGREES C (125 DEGREES F) CLOSE VALVE AFTER EACH USE AND WHEN EMPTY. KEEP VALVE PROTECTIVE CAP IN PLACE WHEN NOT IN USE, IS SO EQUIPPED. USE IN ACCORDANCE WITH RWS MSDS-NIT.

DO NOT REMOVE THIS PRODUCT LABEL MADE IN THE USA PRESSURE__________ PSIG AT 70 F SIZE_____ CONTENTS ____LITERS RETURN WITH 25 PSIG

RWSLB4 REV 01/09 CAS 7727-37-9

NITROGEN REFRIGERATED LIQUID LABEL

NITROGEN REFRIGERATED LIQUID N.F. UN 1977 NON-FLAMMABLE-2

GROSS WT_____LBS OZ NET WT_____LBS OZ SIZE________ CONTENTS_____LITERS

ALWAYS KEEP CONTAINER IN UPRIGHT POSITION DO NOT CHANGE OR FORCE FIT CONNECTIONS

WARNING: EXTREMELY COLD LIQUID AND GAS UNDER PRESSURE. CAN CAUSE RAPID SUFFOCATION. CAN CAUSE SEVERE FROSTBITE. STORE AND USE WITH ADEQUATE VENTILATION. USE ONLY WITH EQUIPMENT DESIGNED FOR NITROGEN SERVICE AND RATED FOR CYLINDER PRESSURE. CONTAINER TEMPERATURE SHOULD NEVER EXCEED 52 DEGREES C (125 DEGREES F) USE A BACK FLOW PREVENTATIVE DEVICE IN THE PIPING. DON NOT GET LIQUID IN EYES, ON SKIN OR CLOTHING. FOR LIQUID WITHDRAWAL WEAR FACE SHIELD AND GLOVES. DO NOT DROP. USE HAND TRUCK SPECIFICALLY DESIGNED FOR LIQUID CYLINDER MOVEMENT. CLOSE VALVE AFTER EACH USE AND WHEN EMPTY. USE IN ACCORDANCE WITH THE RWS MSDS-G045.

DO NOT VENT CYLINDER IN CONFINED SPACES. DO NOT ENTER CONFINED SPACE WHERE GAS MAY BE PRESENT UNLESS AREA HAS BEEN WELL VENTED AND SPACE HAS BEEN TESTED FOR ADEQUATE OXYGEN LEVEL (AT LEAST 19%) WITH AN APPROVED OXYGEN MEASURING INSTRUMENT OR WEARING AN APPROVED AIR SUPPLIED BREATHING APPARATUS WITH A SECOND PERSON PRESENT, SIMILARLY EQUIPPED.

DO NOT REMOVE THIS PRODUCT LABEL CAS 7727-37-9 TO BE REFILLED BY RWS AUTHORIZED FACILITY ONLY RWSLB1 REV 01/09

PRODUCT WARNINGS AND PRECAUTIONS

WARNING: ADMINISTRATION OF NITROGEN MAY BE HAZARDOUS OR CONTRAINDICATED. FOR USE ONLY BY OR UNDER THE SUPERVISION OF A LICENSED PRACTITIONER WHO IS EXPERIENCED IN THE USE AND ADMINISTRATION OF NITROGEN AND IS FAMILIAR WITH THE INDICATION, EFFECTS, DOSAGES, METHODS AND FREQUENCY AND DURATION OF ADMINISTRATION, AND WITH THE HAZARDS, CONTRAINDICATIONS AND SIDE EFFECTS AND THE PRECAUTIONS TO BE TAKEN.

FIRST AID: IF INHALED, REMOVE TO FRESH AIR. IF NOT BREATHING, GIVE ARTIFICIAL RESPIRATION, PREFERABLY MOUTH-TO-MOUTH. IF BREATHING DIFFICULT GIVE OXYGEN. CALL A PHYSICIAN. IN CASE OF FROSTBITE OBTAIN PROFESSIONAL MEDICAL TREATMENT IMMEDIATELY.

RX ONLY